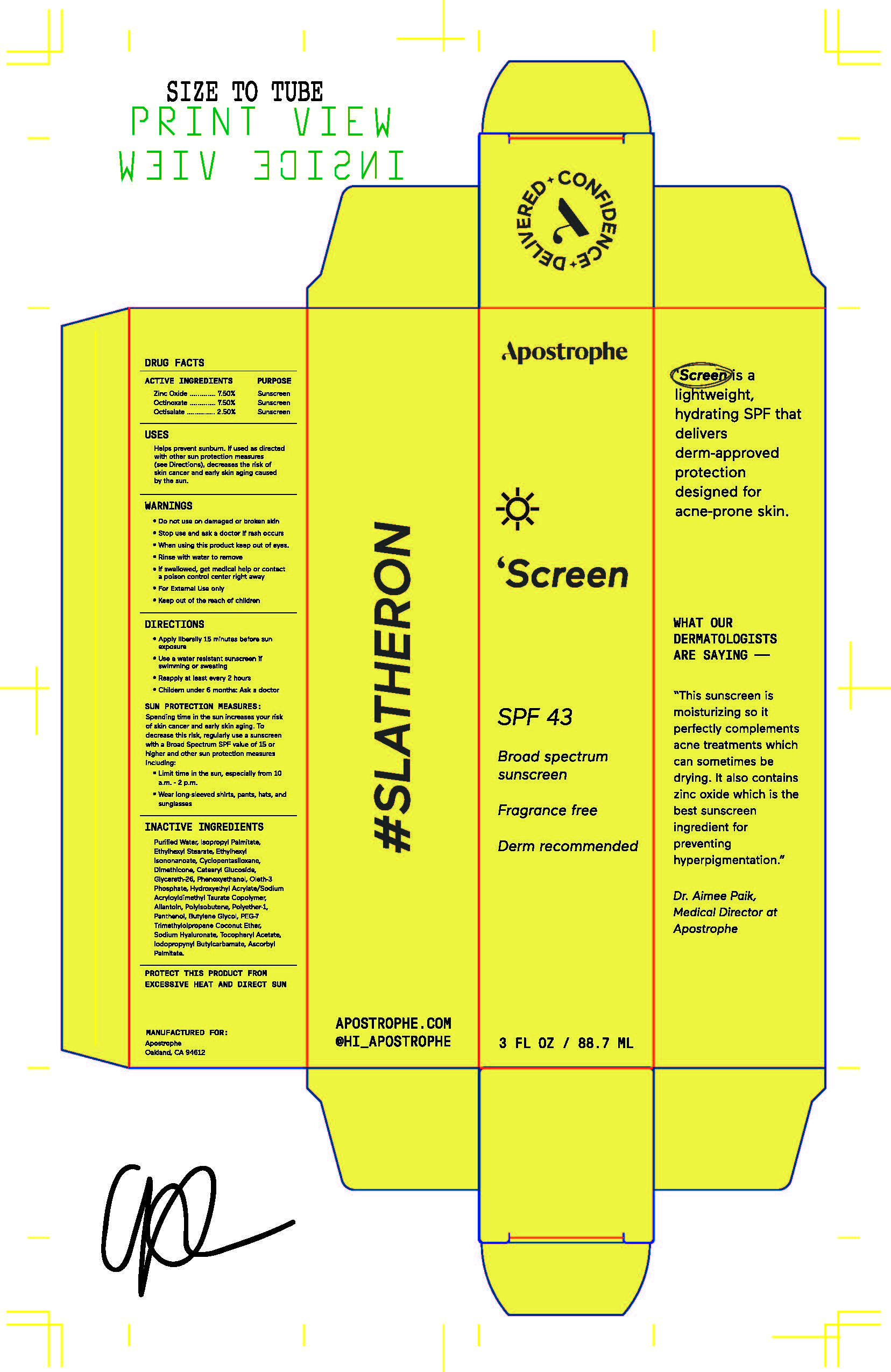 DRUG LABEL: Apostrophe Screen SPF43
NDC: 81780-007 | Form: LOTION
Manufacturer: Yoderm, Inc.
Category: otc | Type: HUMAN OTC DRUG LABEL
Date: 20231107

ACTIVE INGREDIENTS: OCTISALATE 25 g/1000 g; OCTINOXATE 75 g/1000 g; ZINC OXIDE 75 g/1000 g
INACTIVE INGREDIENTS: WATER; ISOPROPYL PALMITATE; ETHYLHEXYL STEARATE; ETHYLHEXYL ISONONANOATE; CYCLOMETHICONE 5; DIMETHICONE; CETEARYL GLUCOSIDE; GLYCERETH-26; PHENOXYETHANOL; OLETH-3 PHOSPHATE; HYDROXYETHYL ACRYLATE/SODIUM ACRYLOYLDIMETHYL TAURATE COPOLYMER (45000 MPA.S AT 1%); ALLANTOIN; POLYISOBUTYLENE (1000 MW); PANTHENOL; BUTYLENE GLYCOL; HYALURONIC ACID; .ALPHA.-TOCOPHEROL ACETATE; IODOPROPYNYL BUTYLCARBAMATE; ASCORBYL PALMITATE; TRIETHOXYCAPRYLYLSILANE

Apostrophe Screen SPF43

Warnings

For external use only. Do not use on damaged or broken skin. When using this product keep out of eyes. Rinse with water to remove. Stop use and ask a physician if rash occurs. If product is swallowed get medical help or contact a Poison Control Center right away.

Active Ingredients

Zinc Oxide 7.5% Sunscreen

Octinoxate 7.5% Sunscreen

Octisalate 2.5% Sunscreen

Uses

Helps prevent sunburn. If used as directed with other sun protection measure (See Directions), decreases the risk of skin cancer and early skin aging caused by the sun.

Uses

Helps prevent sunburn. If used as directed with other sun protection measure (See Directions), decreases the risk of skin cancer and early skin aging caused by the sun.

KEEP OUT OF REACH OF CHILDREN

Directions

Apply liberally 15 minutes before sun exposure. Use a water-resistant sunscreen if swimming or sweating. Reapply at least every 2 hours. Sun Protection Measures: Spending time in the sun increases your risk of skin cancer and early skin aging. To decrease this risk, regularly use a sunscreen with a broad-spectrum SPF of 15 or higher and other sun protection measures including: limit time in the sun, especially from 10 am to 2 pm. Wear long-sleeve shirts, pants, hats, and sunglasses. Children under 6 months: ask a physician.

Other Information

Protect this product from excessive heat and direct sun.

Inactive Ingredients

purified water, isopropyl palmitate, ethylhexyl stearate, ethylhexyl isononanoate, cyclopentasiloxane, dimethicone, cetearyl glucoside, glycereth-26, phenoxyethanol, oleth-3 phosphate, hydroxyethyl acrylate/sodium acryloyldimethyl taurate copolymer, allantoin, polyisobutene, polyether-1, panthenol, butylene glycol, PEG-7 trimethylolpropane coconut ether, sodium hyaluronate, tocopheryl acetate, iodopropynyl butylcarbamate, ascorbyl palmitate, triethoxycaprylylsilane